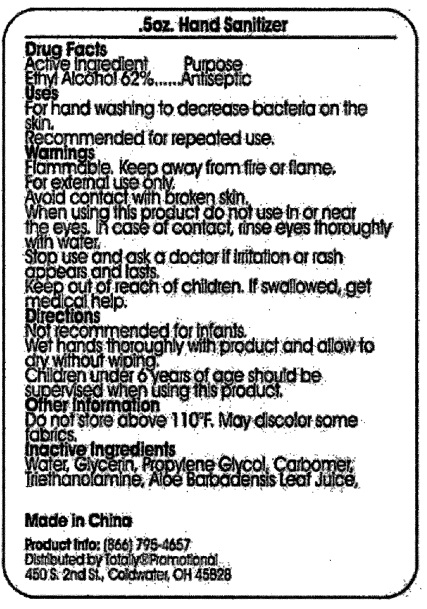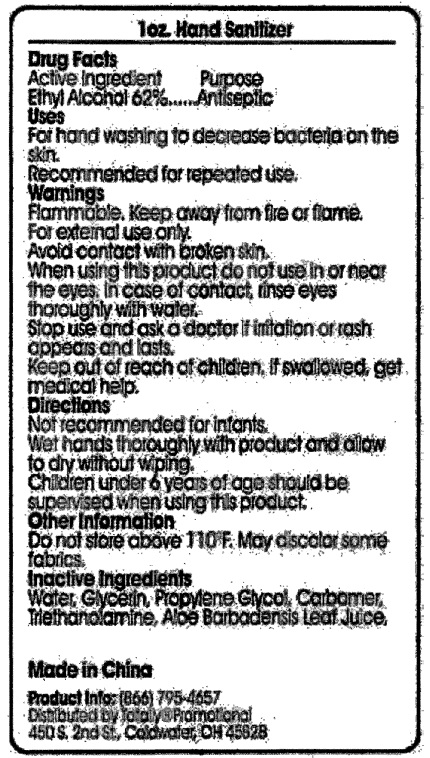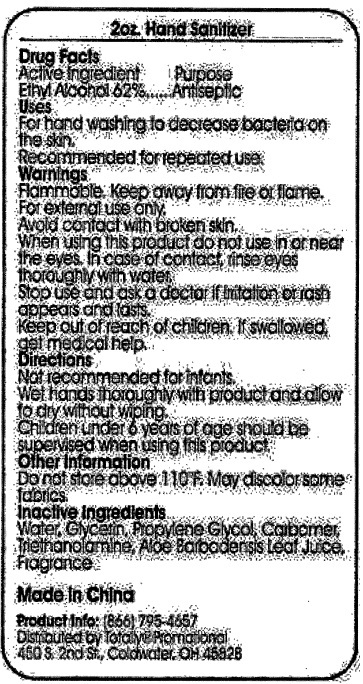 DRUG LABEL: Hand Sanitizer
NDC: 71087-003 | Form: GEL
Manufacturer: CASAD Company, Inc
Category: otc | Type: HUMAN OTC DRUG LABEL
Date: 20241009

ACTIVE INGREDIENTS: ALCOHOL 62 mL/100 mL
INACTIVE INGREDIENTS: WATER; GLYCERIN; PROPYLENE GLYCOL; CARBOMER 934; TROLAMINE; ALOE VERA LEAF

Hand Sanitizer 0.5 OZ, 1 OZ, 2 OZ

Drug Facts Active Ingredient

Ethyl Alcohol 62%

Purpose

Antiseptic

Use

For hand washing to decrease bacteria on the skin. Recommended for repeated use.

Warnings

Flammable. Keep away from fire and flame. For external use only. Avoid contact with broken skin. When using this product do not use in or near the eyes. In case of contact, rinse eyes thoroughly with water. Stop use and ask a doctor if irritation or rash appears and lasts.

Keep out of reach of children

If swallowed, get medical help.

Directions

Not recommended for infants. Wet hands thoroughly with product and allow to dry without wiping. Children under 6 years of age should be supervised when using this product

Other Information

Do not store above 110°F. May discolor some fabrics.

Inactive Ingredients

Water, Glycerin, Propylene Glycol, Carbomer, Triethanolamine, Aloe Barbadensis Leaf juise

Hand Sanitizer Unscented product label

Hand Sanitizer Unscented

Made in China

Product Info: (866) 795-4657
Distributed by Totally®Promotional
450 S. 2nd Sr., Coldwater, OH 45828

0.5 oz. Hand Sanitizer

1 oz. Hand Sanitizer

2 oz. Hand Sanitizer

res